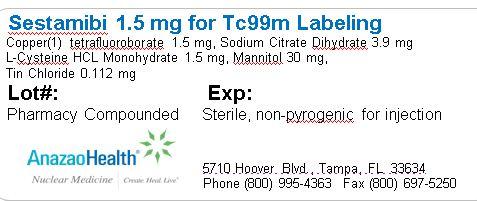 DRUG LABEL: Sestamibi
NDC: 51808-208 | Form: INJECTION, POWDER, LYOPHILIZED, FOR SOLUTION
Manufacturer: AnazaoHealth Corporation
Category: prescription | Type: HUMAN PRESCRIPTION DRUG LABEL
Date: 20120523

ACTIVE INGREDIENTS: TETRAKIS(2-METHOXYISOBUTYLISOCYANIDE)COPPER(I) TETRAFLUOROBORATE 1.5 mg/1 1
INACTIVE INGREDIENTS: TRISODIUM CITRATE DIHYDRATE 3.9 mg/1 1; CYSTEINE HYDROCHLORIDE 1.5 mg/1 1; MANNITOL 30 mg/1 1; STANNOUS CHLORIDE 0.112 mg/1 1

Sestamibi
(for the preparation of Tc99m Sestamibi injection)

Dear Medical Professional,

Per your order, we have compounded Sestamibi as a sterile, freeze-dried preparation in a 10 mL vial. The characteristics of this preparation are described below.

DESCRIPTION

AnazaoHealth’s compounded Sestamibi vial is a sterile, non-pyrogenic preparation that consists of a lyophilized mixture of 1.5mg of Copper (1) tetrafluoroborate, 3.9 mg of Sodium Citrate Dihydrate, 1.5 mg of L-Cysteine HCL Monohydrate, 30 mg Mannitol and 0.112 mg of Tin Chloride. It is maintained under an inert nitrogen atmosphere. Prior to lyophilization the pH is 5.3 to 5.9. The pH of the final reconstituted product is 5.5 to 6.0. It contains no antimicrobrial preservative.

CLINICAL PHARMACOLOGY

When Sestamibi is reconstituted with Tc99m pertechnetate, a complex of Tc99m Sestamibi is formed and is the active ingredient of the reconstituted product. When administered intravenously, Tc99m Sestamibi shows rapid myocardial uptake and its distribution follows a linear relationship with coronary blood flow.

Tc99m Sestamibi is a lipophilic agent that is taken up by the mitochondria of myocardial cells by passive diffusion and appears to accumulate in viable myocardial tissue.

INDICATIONS AND USAGE

Sestamibi is a diagnostic agent used to assess areas of reversible myocardial ischemia in the presence or absence of infracted myocardium. Evaluation of myocardial ischemia can be accomplished with rest and cardiovascular stress techniques.

PREPARATION

Instructions for the preparation of Tc99m Sestamibi

1. Inspect vial to ensure there are no cracks in the glass.

2. Reconstitute with 1- 3ml of non-pyrogenic, oxidant free Sodium Pertechnetate Tc99m injection.

3. Remove equal amount of inert gas from vial and shake vigorously 10 times.

4. Place vial in a boiling water bath for 10 minutes beginning when the bath begins boiling again.

5. Do not allow water to come in contact with aluminum crimp.

1. Remove vial from water bath place in lead shield and allow to cool for 15 minutes
2. Behind appropriate shielding visually inspect the contents of the vial. Contents should be clear and free of particulate matter.
3. pH of the final reconstituted product is 5.5 to 6.0.
4. This vial contains no preservatives - contents should be used within 6 hours.
5. Store shielded vial at 15-25 degrees Celsius until use and withdraw dose aseptically.

Instructions for the determination of radiochemical purity in Tc99m Sestamibi

1. Dry a pre-cut 2.5cm X 7.5cm Baker-Flex Aluminum Oxide coated, plastic TLC #1 B-F Plate
  at 100 degrees Celsius for 1 hour and store in a desiccator. Remove strip just prior to use.
2. Apply one drop of Ethanol using a 1ml syringe with a 22-26guage needle 1.5cm from the bottom of the plate. Do not allow to dry.
3. Put two drops of Tc99m Sestamibi side by side on top to the Ethanol then return plate to desiccator and allow to dry (typically 15 minutes).
4. Prepare the TLC take by pouring Ethanol to a depth of 3-4 cm then cover the tank and let equilibrate for 10 minutes.
5. Develop the plate in the covered TLC tank, in Ethanol, for a distance of 5cm from the point of application.
6. Cut the TLC plate 4cm from the bottom and measure the Tc99m activity in each piece with appropriate radiation detector.
7. Calculate the % Tc99m Sestamibi as:
  Activity top piece (front)/ Activity both pieces (origin + front) x 100

Storage and Handling

This preparation is recommended to be stored in the refrigerator prior to reconstitution..

PACKAGE LABEL.PRINCIPAL DISPLAY PANEL

Figure 1